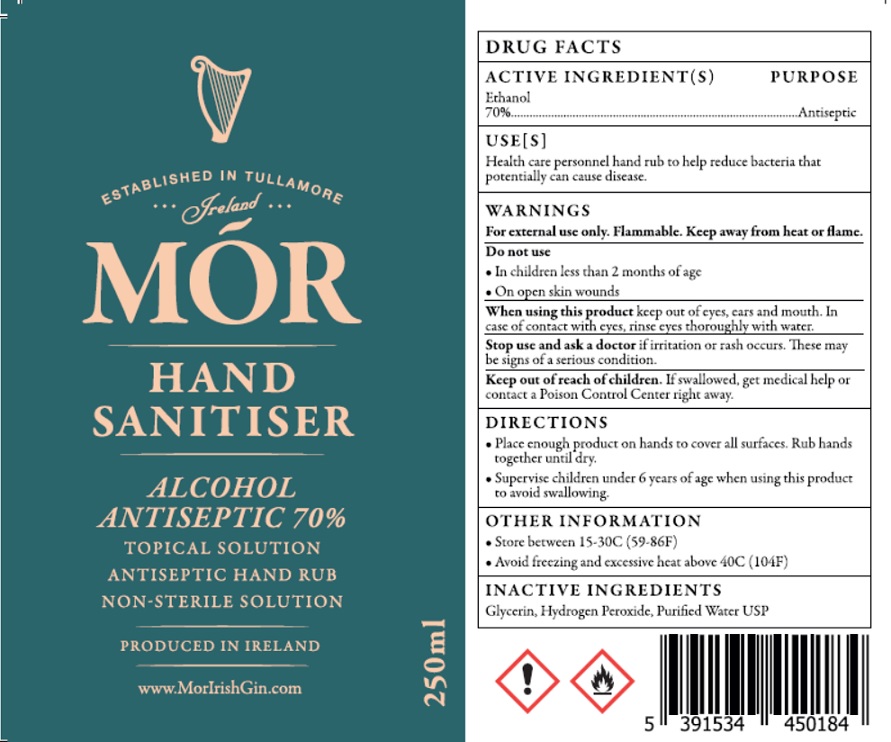 DRUG LABEL: MOR HAND SANITIZER
NDC: 78375-001 | Form: SOLUTION
Manufacturer: ARDERIN DISTILLERY LIMITED
Category: otc | Type: HUMAN OTC DRUG LABEL
Date: 20200526

ACTIVE INGREDIENTS: ALCOHOL 70 mL/100 mL
INACTIVE INGREDIENTS: GLYCERIN; HYDROGEN PEROXIDE; WATER

MOR HAND SANITIZER

ACTIVE INGREDIENT(S)

Ethanol 70%

PURPOSE

Antiseptic

USE[S]

Health care personnel hand rub to help reduce bacteria that potentially can cause disease.

WARNINGS

For external use only. Flammable. Keep away from heat or flame.

Do not use

- In children less than 2 months of age
- On open skin wounds

When using this product keep out of eyes, ears and mouth. In case of contact with eyes, rinse eyes thoroughly with water.

Stop use and ask a doctor if irritation or rash occurs. These may be signs of a serious condition.

Keep out of reach of children. If swallowed, get medical help or contact a Poison Control Center right away.

DIRECTIONS

- Place enough product on hands to cover all surfaces. Rub hands together until dry.
- Supervise children under 6 years of age when using this product to avoid swallowing.

OTHER INFORMATION

- Store between 15-30C (59-86F)
- Avoid freezing and excessive heat above 40C (104F)

INACTIVE INGREDIENTS

Glycerin, Hydrogen Peroxide, Purified Water USP

ESTABLISHED IN TULLAMORE

Ireland

ANTISEPTIC HAND RUB

NON-STERILE SOLUTION

PRODUCED IN IRELAND

www.MorIrishGin.com